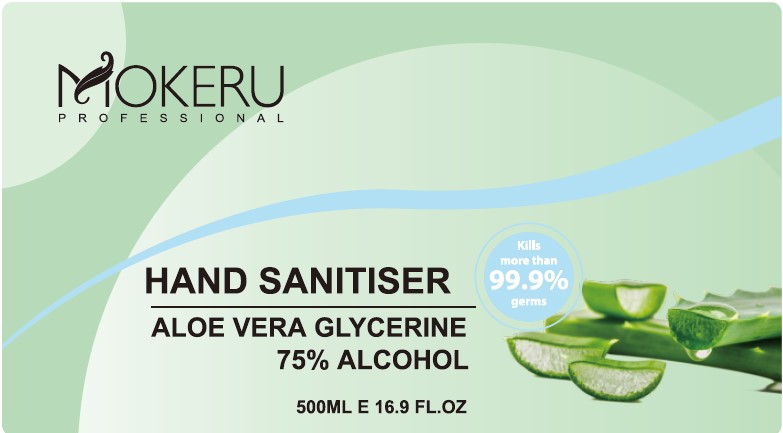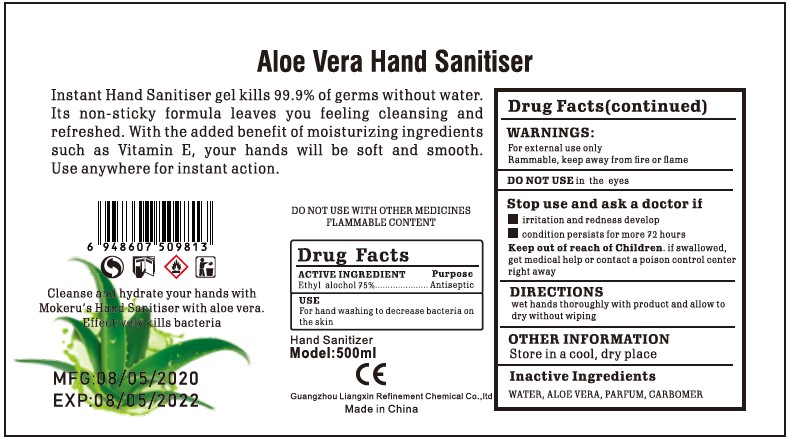 DRUG LABEL: Hand Sanitizer
NDC: 76861-001 | Form: GEL
Manufacturer: Guangzhou Liangxin Refinement Chemical Co.,ltd
Category: otc | Type: HUMAN OTC DRUG LABEL
Date: 20200506

ACTIVE INGREDIENTS: ALCOHOL 75 mL/100 mL
INACTIVE INGREDIENTS: CARBOMER HOMOPOLYMER, UNSPECIFIED TYPE 0.2 mL/100 mL; ALOE VERA LEAF 0.8 mL/100 mL; WATER

hand sanitiser

Active Ingredient(s)

Ethyl alcohol 75% Purpose: Antiseptic

Purpose

Antiseptic, Hand Sanitizer

Use

For hand washing to decrease bacteria on the skin

Warnings

For external use only. Flammable. Keep away from heat or flame

Do not use

in the eyes

When using this product keep out of eyes, ears, and mouth. In case of contact with eyes, rinse eyes thoroughly with water.
Stop use and ask a doctor if irritation or rash occurs. These may be signs of a serious condition.
Keep out of reach of children. If swallowed, get medical help or contact a Poison Control Center right away.

stop use and ask a doctor if

irritation and redness develop

condition persists for more 72hours

Keep out of reach of children. If swallowed, get medical help or contact a Poison Control Center right away.

Directions

wet hands thoroughly with product and allow to dry without wiping

Other information

Store in a cool,dry place

Inactive ingredients

water,aloe vera,parfum,carbomer

Package Label - Principal Display Panel

500 mL NDC: 76861-001-01